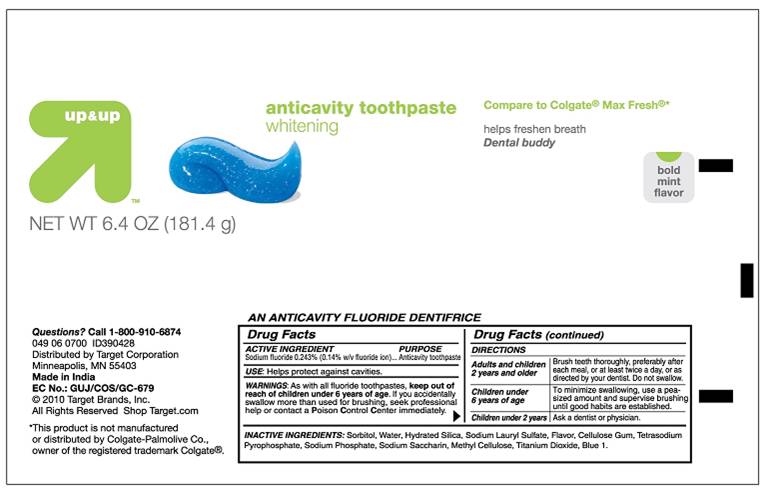 DRUG LABEL: Up and Up Anticavity Toothpaste Whitening 
NDC: 67659-082 | Form: PASTE, DENTIFRICE
Manufacturer: Team Technologies, Inc
Category: otc | Type: HUMAN OTC DRUG LABEL
Date: 20100825

ACTIVE INGREDIENTS: SODIUM FLUORIDE 2.43 mg/1 g
INACTIVE INGREDIENTS: SORBITOL; WATER; SILICON DIOXIDE; SODIUM LAURYL SULFATE; CROSCARMELLOSE SODIUM; SODIUM PYROPHOSPHATE; SODIUM PHOSPHATE; SACCHARIN SODIUM; TITANIUM DIOXIDE; FD&C BLUE NO. 1

Up and Up anticavity toothpaste whitening

Active Ingredients

Sodium Fluoride 0.243% (0.14% w/v fluoride ion)... Anticavity toothpaste

USE

Helps protect against cavities

WARNINGS

As with all fluoride toothpastes, keep out of reach of children under 6 years of age. If you accidentally swallow more than used for brushing, seek professional help or contact a Poison Control Center immediately.

Directions

Adults and children 2 years and older Brush teeth throughly, preferably after each meal, or at least twice a day, or as directed by your dentist. Do not swallow.
Children under 6 years of age To minimize swallowing, use a pea-sized amount and supervise brushing until good habits are established.
Children under 2 years Ask a dentist or physician

Inactive ingredients:

Sorbitol, Water, Hydrated Silica, Sodium Lauryl Sulfate, Flavor, Cellulose Gum, Tetrasodium Pyrophosphate, Sodium Phosphate, Sodium Saccharin, Methyl Cellulose, Titanium Dioxide, Blue 1.

PURPOSE

Anticavity toothpaste

KEEP OUT OF REACH OF CHILDREN